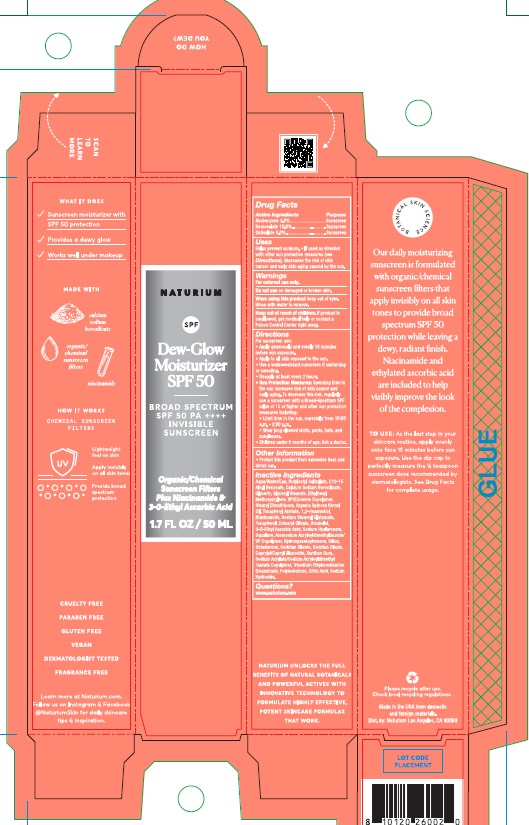 DRUG LABEL: Naturium Dew-Glow Moisturizer SPF 50
NDC: 76354-130 | Form: LOTION
Manufacturer: e.l.f. Cosmetics, Inc
Category: otc | Type: HUMAN OTC DRUG LABEL
Date: 20251114

ACTIVE INGREDIENTS: HOMOSALATE 100 mg/1 mL; OCTISALATE 50 mg/1 mL; AVOBENZONE 30 mg/1 mL
INACTIVE INGREDIENTS: SODIUM ACRYLATE/SODIUM ACRYLOYLDIMETHYLTAURATE COPOLYMER (4000000 MW); TRISODIUM ETHYLENEDIAMINE DISUCCINATE; POLYISOBUTYLENE (55000 MW); LEVOMENOL; 3-O-ETHYL ASCORBIC ACID; NIACINAMIDE; CETEARYL OLIVATE; AMMONIUM ACRYLOYLDIMETHYLTAURATE/VP COPOLYMER; SODIUM STEAROYL GLUTAMATE; VINYLPYRROLIDONE/EICOSENE COPOLYMER; ETHYLHEXYL METHOXYCRYLENE; STEARYL DIMETHICONE (400 MPA.S AT 50C); SILICON DIOXIDE; SORBITAN OLIVATE; GLYCERYL MONOSTEARATE; WATER; BUTYLOCTYL SALICYLATE; GLYCERIN; SORBITAN MONOOLEATE; ARGAN OIL; HYDROXYACETOPHENONE; OCTADECENE; CAPRYLYL/CAPRYL OLIGOGLUCOSIDE; XANTHAN GUM; ALKYL (C12-15) BENZOATE; BOROSILICATE GLASS; 1,2-HEXANEDIOL; ANHYDROUS CITRIC ACID; SQUALANE; TOCOPHEROL; SODIUM HYDROXIDE; HYALURONATE SODIUM; .ALPHA.-TOCOPHEROL ACETATE

Naturium Dew-Glow Moisturizer SPF 50

Active Ingredients

Avobenzone 3.0%

Homosalate 10.0%

Octisalate 5.0%

Purpose

Sunscreen

Uses

- Helps prevent sunburn.
- If used as directed with other sun protection measures (see Directions), decreases the risk of skin cancer and early skin aging caused by the sun.

Warnings

For external use only.

Do not use

on damaged or broken skin.

When using this product

keep out of eyes. Rinse with water to remove.

Keep out of reach of children.

If product is swallowed, get medical helkp or contact a Poison Control Center right away.

Directions

For sunscreen use:

- Apply generously and evenly 15 minutes before sun exposure.
- Apply to all skin exposed to the sun.
- Use a water-resistant sunscreen if swimming or sweating.
- Reapply at least every 2 hours.
- Sun Protection Measures: Spending time in the sun increases risk of skin cancer and early aging. To decrease this risk, regularly use a sunscreen with a Broad-Spectrum SPF value of 15 or higher and other sun protection measures including:
- Limit time in the sun, especially from 10:00 a.m. - 2:00 p.m.
- Wear long sleeved shirts, pants, hats, and sunglasses.
- Children under 6 months of age: Ask a doctor.

Other Information

- Protect this product from excessive heat and direct sun.

Inactive Ingredients

Aqua/Water/Eau, Butyloctyl Salicylate, C12-15 Alkyl Benzoate, Calcium Sodium Borosilicate, Glycerin, Glyceryl Stearate, Ethylhexyl Methoxycrylene, VP/Eicosene Copolymer, Stearyl Dimethicone, Argania Spinosa Kernel Oil, Tocopheryl Acetate, 1,2-Hexandiol, Niacinamide, Sodium Stearoyl Glutamate, Tocopherol, Cetearyl Olivate, Bisabolol, 3-O-Ethyl Ascorbic Acid, Sodium Hyaluronate, Squalane, Ammonium Acryloyldimethyltaurate/VP Copolymer, Hydroxyacetophnone, Silica, Octadecene, Sorbitan Olivate, Sorbitan Oleate, Caprylyl/Capryl Glucoside, Xanthan Gum, Sodium Acrylate/Sodium Acryloyldimethyltaurate/VP Copolymer, Hydroxyacetophenone, Silica, Octadecene, Sorbitan Olivate, Sorbitan Oleate, Caprylyl/Capryl Glucoside, Xanthan Gum, Sodium Acrylate/Sodium Acryloyldimethyl Taurate Copolymer, Trisodium Ethylenediamine Disuccinate, Polyisobutene, Citric Acid, Sodium Hydroxide.

Questions?

www.naturium.com